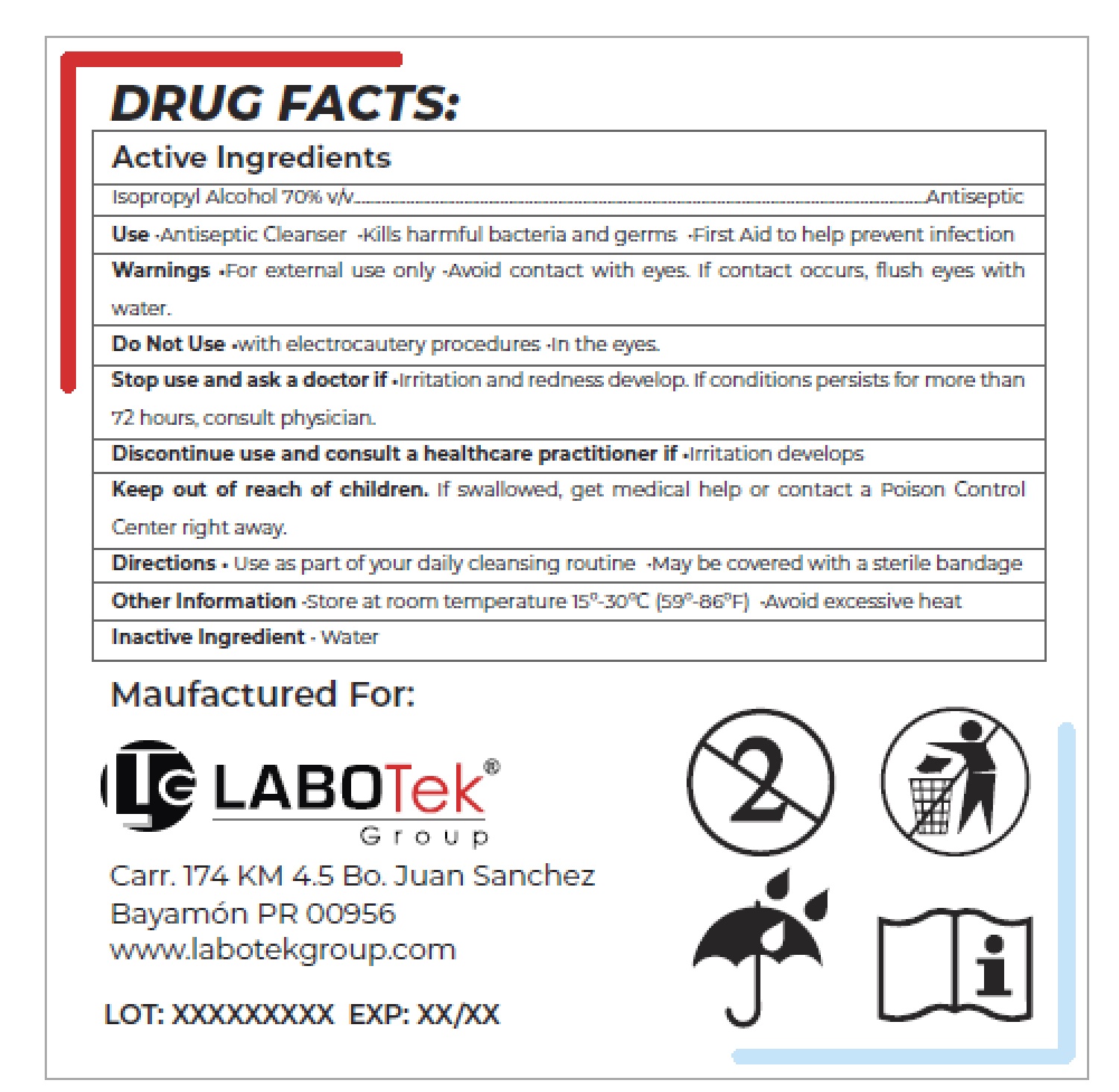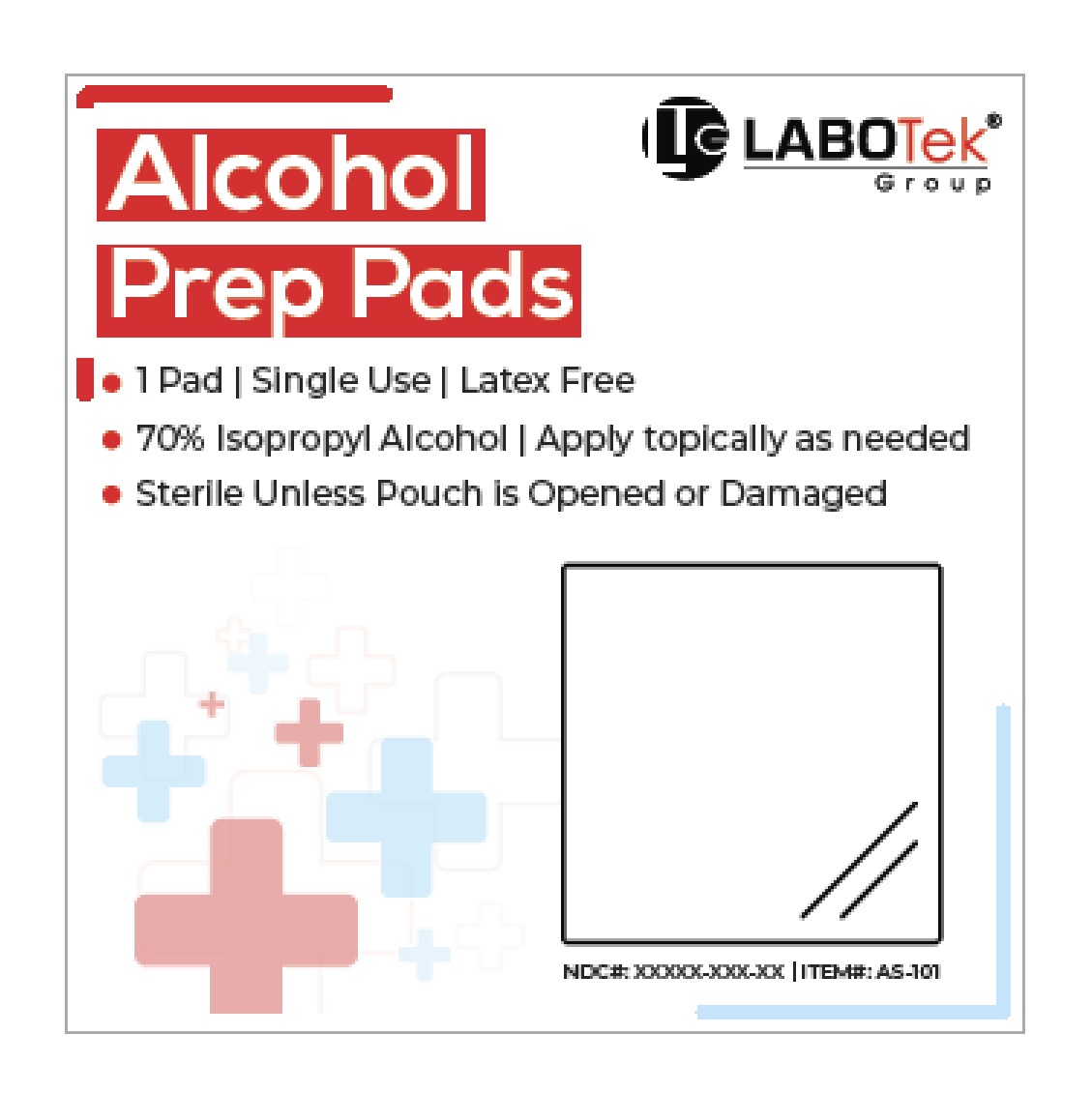 DRUG LABEL: LTG Alcohol Prep Pads
NDC: 81264-001 | Form: CLOTH
Manufacturer: Labotek Group Corp
Category: otc | Type: HUMAN OTC DRUG LABEL
Date: 20201217

ACTIVE INGREDIENTS: ISOPROPYL ALCOHOL 70 mL/100 mL
INACTIVE INGREDIENTS: WATER

LTG Alcohol Prep Pads

Active Ingredients

Isopropyl Alcohol 70% v/v

Purpose

Antiseptic

Use

•Antiseptic Cleanser •Kills harmful bacteria and germs •First Aid to help prevent infection

Warnings

•For external use only •Avoid contact with eyes. If contact occurs, flush eyes with water.

Do Not Use

•with electrocautery procedures •In the eyes.

Stop use and ask a doctor if

•Irritation and redness develop. If conditions persists for more than 72 hours, consult physician.

Discontinue use and consult a healthcare practitioner if •Irritation develops

Keep out of reach of children.

If swallowed, get medical help or contact a Poison Control Center right away.

Directions

- Use as part of your daily cleansing routine
- May be covered with a sterile bandage

Other Information

•Store at room temperature 15º-30ºC (59º-86ºF) •Avoid excessive heat

Inactive Ingredient

• Water